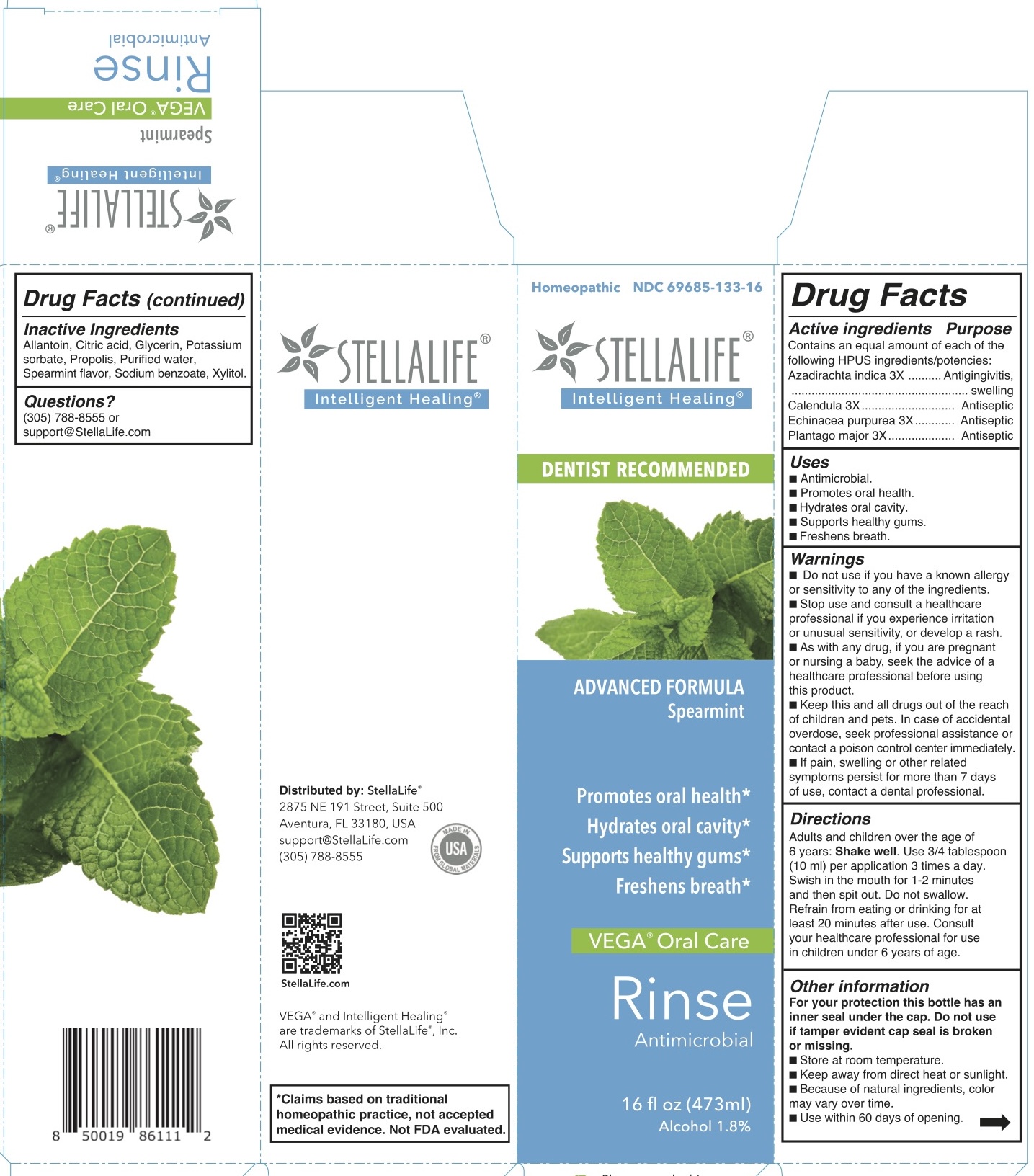 DRUG LABEL: StellaLife VEGA Oral Care Spearmint
NDC: 69685-133 | Form: RINSE
Manufacturer: StellaLife, Inc.
Category: homeopathic | Type: HUMAN OTC DRUG LABEL
Date: 20251222

ACTIVE INGREDIENTS: PLANTAGO MAJOR 3 [hp_X]/1 mL; AZADIRACHTA INDICA BARK 3 [hp_X]/1 mL; CALENDULA OFFICINALIS FLOWER 3 [hp_X]/1 mL; ECHINACEA PURPUREA 3 [hp_X]/1 mL
INACTIVE INGREDIENTS: XYLITOL; ALCOHOL; SPEARMINT; CITRIC ACID MONOHYDRATE; GLYCERIN; SODIUM BENZOATE; POTASSIUM SORBATE; WATER; ALLANTOIN; PROPOLIS WAX

Rinse - Spearmint - SellaLife

Active Ingredients

Azadirachta indica 3X
Calendula 3X
Echinacea purpurea 3X
Plantago major 3X

Purpose

Active ingredient | Purpose
Azadirachta indica | Antigingivitis, swelling
Calendula | Antiseptic
Echinacea purpurea | Antiseptic
Plantago major | Antiseptic

Uses

■ Antimicrobial.

■ Promotes oral health.

■ Hydrates oral cavity.

■ Supports healthy gums.

■ Freshens breath.

Directions

Adults and children over the age of 6 years: Shake well. Use 3/4 tablespoon (10 ml) per application 3 times a day or as recommended by a dental professional. Swish in the mouth for 1-2 minutes and then spit out. Do not swallow. Refrain from eating or drinking for at least 20 minutes after use. Consult your healthcare professional for use in children under 6 years of age.

Keep out of reach of children

■ Keep this and all drugs out of the reach of children and pets. In case of accidental overdose, seek professional assistance or contact a poison control center immediately.

Pregnancy and breast feeding

■ As with any drug, if you are pregnant or nursing a baby, seek the advice of a healthcare professional before using this product.

Other information

■ Store at room temperature.

■ Keep away from direct heat or sunlight.

■ Because of natural ingredients, color may vary over time.

■ Use within 60 days of opening.

Warnings

For your protection, this bottle has an inner seal under the cap. Do not use if tamper evident cap seal is broken or missing.

Stop use

■ Stop use and consult a healthcare professional if you experience irritation or unusual sensitivity, or develop a rash.

ASK DOCTOR

■ If pain, swelling or other related symptoms persist for more than 7 days of use, contact a dental professional.

Inactive Ingredients

Alcohol, Allantoin, Citric acid, Glycerin, Potassium sorbate, Propolis, Purified water, Sodium benzoate, Spearmint flavor, Xylitol.

Questions?

(305) 788-8555 or
support@StellaLife.com